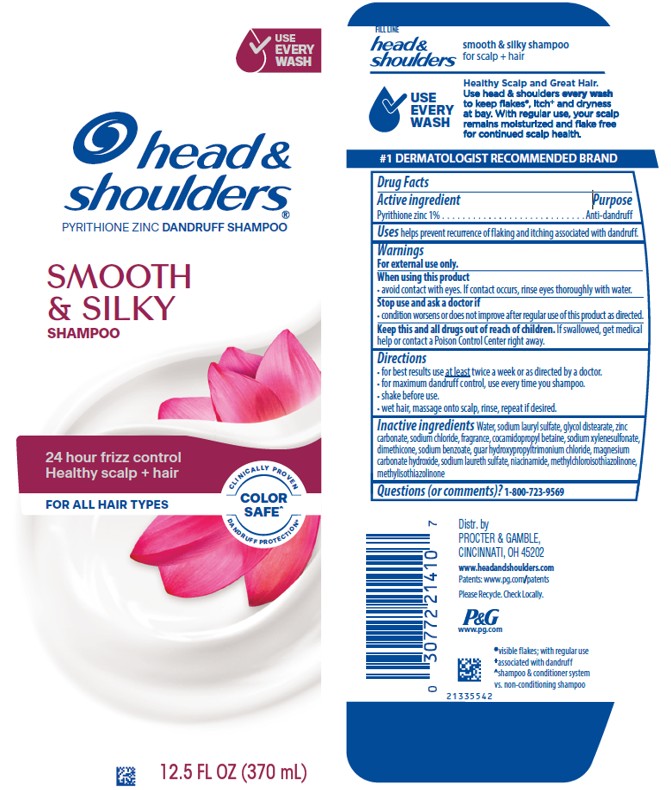 DRUG LABEL: Head and Shoulders
NDC: 37000-094 | Form: LOTION/SHAMPOO
Manufacturer: The Procter & Gamble Manufacturing Company
Category: otc | Type: HUMAN OTC DRUG LABEL
Date: 20260218

ACTIVE INGREDIENTS: PYRITHIONE ZINC 1 g/100 mL
INACTIVE INGREDIENTS: COCAMIDOPROPYL BETAINE; SODIUM LAURYL SULFATE; GUAR HYDROXYPROPYLTRIMONIUM CHLORIDE (1.7 SUBSTITUENTS PER SACCHARIDE); ZINC CARBONATE; WATER; SODIUM LAURETH SULFATE; GLYCOL DISTEARATE; DIMETHICONE; SODIUM XYLENESULFONATE; SODIUM CHLORIDE; SODIUM BENZOATE; MAGNESIUM CARBONATE HYDROXIDE; METHYLCHLOROISOTHIAZOLINONE; METHYLISOTHIAZOLINONE; NIACINAMIDE

Head and Shoulders®
Smooth and Silky

Drug Facts

Active ingredient

Pyrithione zinc 1%

Purpose

Anti-dandruff

Uses

helps prevent recurrence of flaking and itching associated with dandruff.

Warnings

For external use only.

When using this product

- avoid contact with eyes. If contact occurs, rinse eyes thoroughly with water.

Stop use and ask a doctor if

- condition worsens or does not improve after regular use of this product as directed.

KEEP OUT OF REACH OF CHILDREN

Keep this and all drugs out of reach of children. If swallowed, get medical help or contact a Poison Control Center right away.

Directions

- for best results use at least twice a week or as directed by a doctor.
- for maximum dandruff control, use every time you shampoo.
- shake before use.
- wet hair, massage onto scalp, rinse, repeat if desired.

Inactive ingredients

Water, sodium lauryl sulfate, glycol distearate, zinc carbonate, sodiumchloride, cocamidopropyl betaine, fragrance, sodium xylenesulfonate, dimethicone, sodium benzoate, guar hydroxypropyltrimonium chloride, magnesium carbonate hydroxide, sodium laureth sulfate, niacinamide, methylchloroisothiazolinone, methylisothiazolinone

Questions (or comments)?

1-800-723-9569

Dist. by PROCTER & GAMBLE,
CINCINNATI, OH 45202

PRINCIPAL DISPLAY PANEL - 370 mL Bottle Label

head &

shoulders®
pyrithione zinc dandruff shampoo

SMOOTH

& SILKY

SHAMPOO

24 hour frizz control

Health scalp + hair

CLINICALLY PROVEN

COLOR SAFE^+

DANDRUFF PROTECTION*
12.5 FL OZ
370 mL